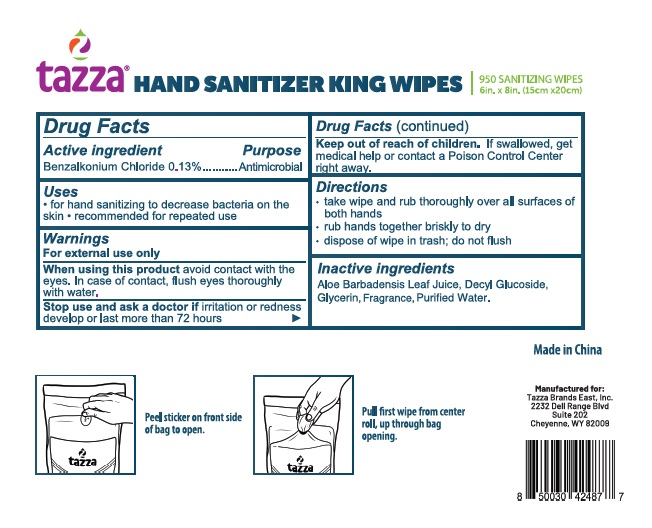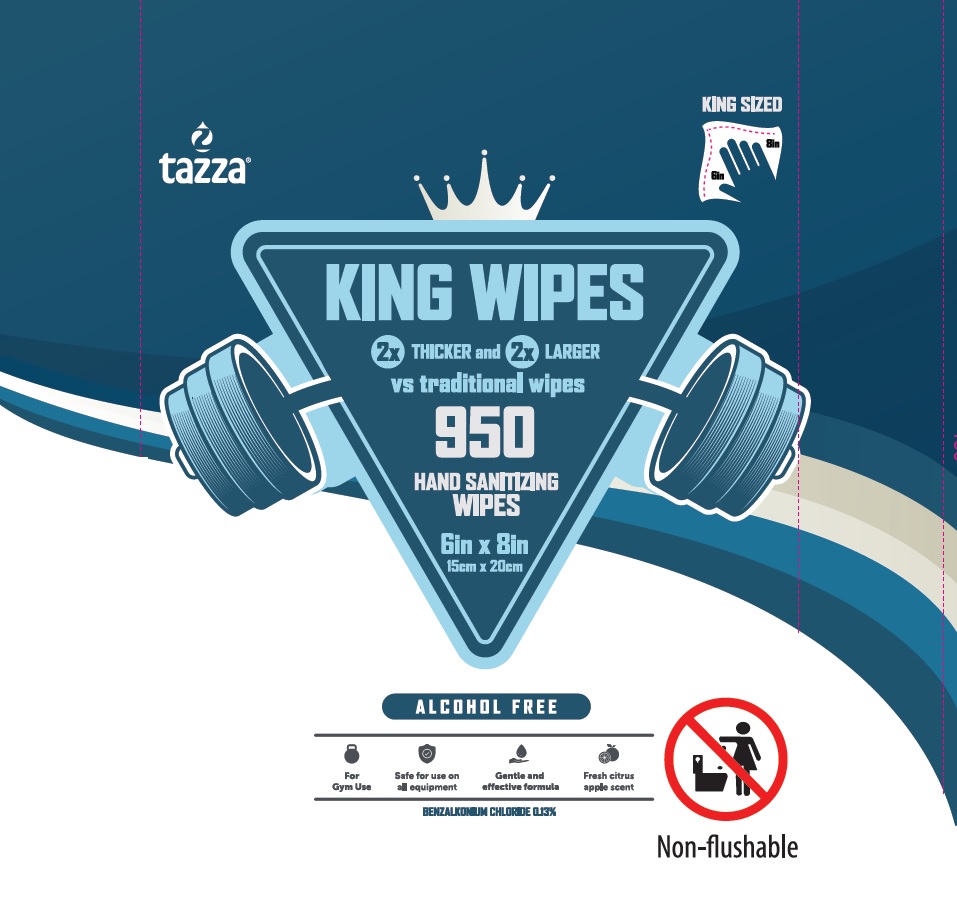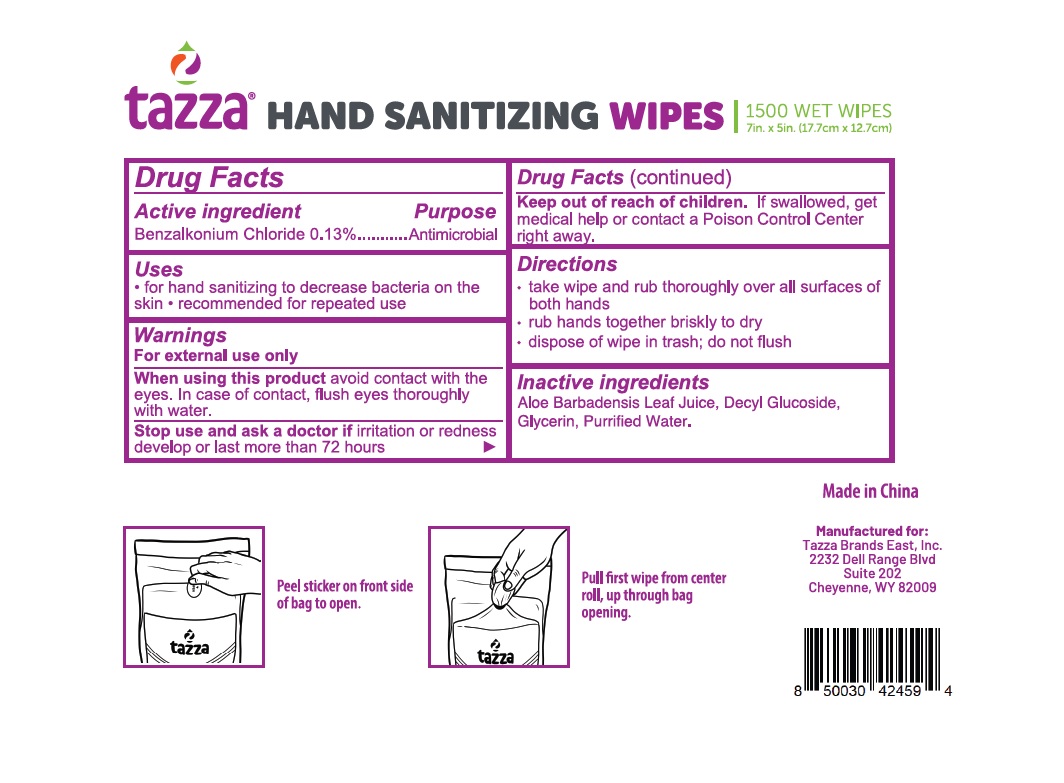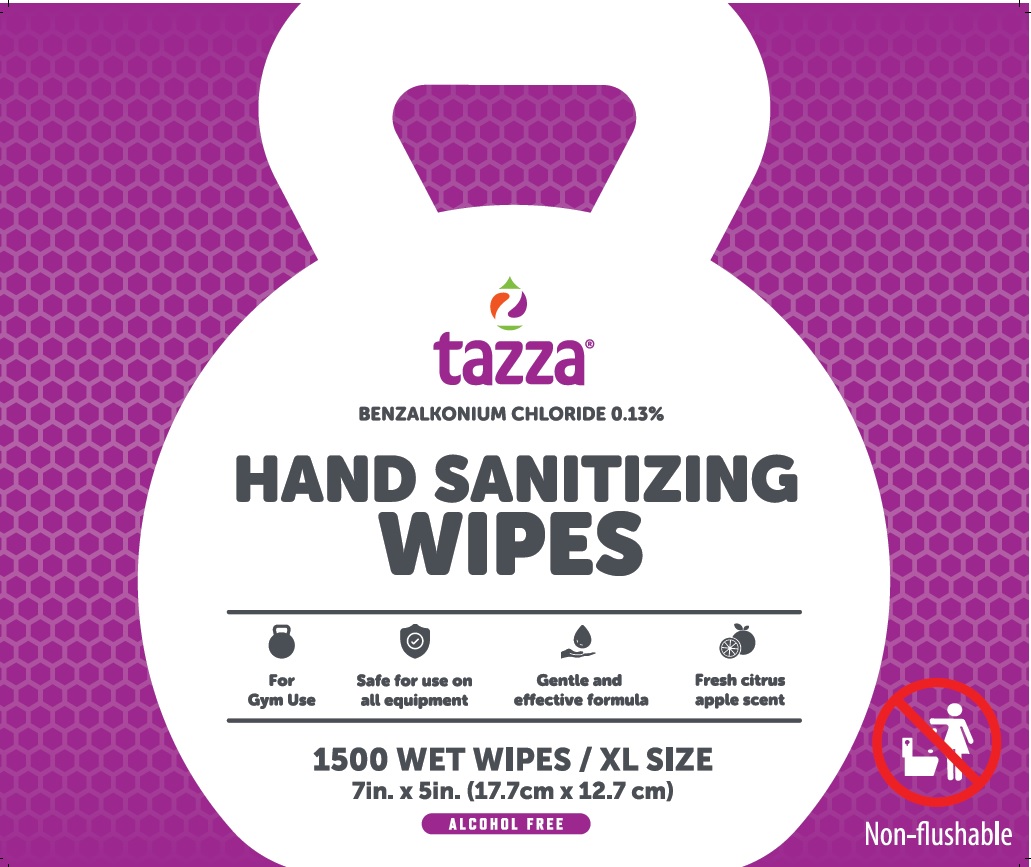 DRUG LABEL: Tazza XL Wipes
NDC: 76370-0025 | Form: CLOTH
Manufacturer: Tazza Brands East Inc.
Category: otc | Type: HUMAN OTC DRUG LABEL
Date: 20240306

ACTIVE INGREDIENTS: BENZALKONIUM CHLORIDE 0.13 g/100 mL
INACTIVE INGREDIENTS: GLYCERIN; WATER; ALOE VERA LEAF; DECYL GLUCOSIDE

Tazza King Wipes 950 ct / Gym Wipes XL1500 ct

Drug Facts

Active ingredient

Benzalkonium Chloride 0.13%

Purpose

Antimicrobial

Uses

- for hand sanitizing to decrease bacteria on the skin
- recommended for repeated use

Warnings

For external use only

When using this product avoid contact with the eyes. In case of eye contact, flush eyes thoroughly with water.

Stop use and ask a doctor if irritation or redness develop or last more than 72 hours

Keep out of reach of children. If swallowed, get medical help or contact a Poison Control Center right away.

Directions

- take wipe and rub thoroughly over all surfaces of both hands
- rub hands together briskly to dry
- dispose of wipe in trash; do not flush

INACTIVE INGREDIENT

Inactive ingredients Aloe barbadensis leaf juice, decyl glucoside, glycerin, fragrance, purified water.

King Wipes

tazza® HAND SANITIZER KING WIPES

950 SANITIZING WIPES

6in x 8in (15cm x 20cm)

Manufactured for:

Tazza Brands East, Inc.
2232 Dell Range Blvd

Suie 202

Cheyenne, WY 82009

Made in China

Gymp Wipes XL

tazza® HAND SANITIZING WIPES

1500 WET WIPES

7in x 5in (17.7cm x 12.7cm)

Manufactured for:

Tazza Brands East, Inc.

2232 Dell Range Blvd, Suite 202

Cheyenne, WY 82009

Made in China

King Wipes

tazza®

KING WIPES

950 HAND SANITIZING WIPES

6in x 8in

15cm x 20cm

ALCOHOL FREE

Benzalkonium Chloride 0.13%

Non-flushable

Gymp Wipes XL

tazza®

BENZALKONIUM CHLORIDE 0.13%

HAND SANITIZING WIPES

1500 WET WIPES / XL SIZE

7in. x 5in. (17.7cm x 12.7cm)

ALCOHOL FREE

Non-flushable